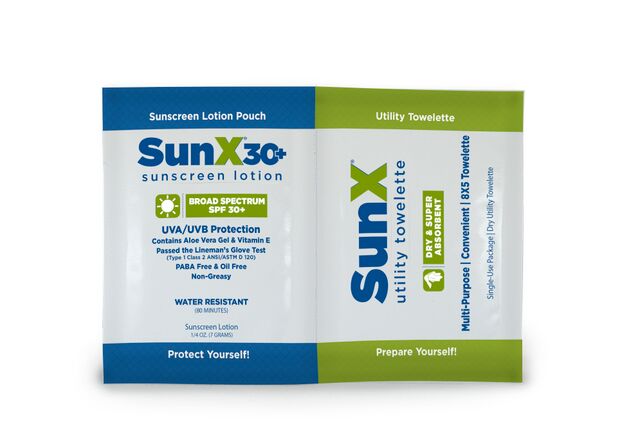 DRUG LABEL: Sun X Multi-Pack SPF 30 Thick
NDC: 65753-102 | Form: LOTION
Manufacturer: CoreTex Products Inc
Category: otc | Type: HUMAN OTC DRUG LABEL
Date: 20200101

ACTIVE INGREDIENTS: AVOBENZONE 1 g/100 g; HOMOSALATE 5 g/100 g; OCTINOXATE 7.5 g/100 g; OCTISALATE 5 g/100 g; OXYBENZONE 6 g/100 g
INACTIVE INGREDIENTS: METHYLPARABEN; C12-20 ALKYL BENZOATE; EDETATE SODIUM; CARBOMER INTERPOLYMER TYPE A (ALLYL SUCROSE CROSSLINKED); ALOE VERA LEAF; PHENOXYETHANOL; CARBOMER HOMOPOLYMER TYPE C (ALLYL PENTAERYTHRITOL CROSSLINKED); ALPHA-TOCOPHEROL ACETATE; DIMETHICONE; ETHYLPARABEN; .ALPHA.-TOCOPHEROL; TROLAMINE; PEG-100 STEARATE; CARBOMER HOMOPOLYMER TYPE A (ALLYL PENTAERYTHRITOL CROSSLINKED); WATER; PROPYLPARABEN; BUTYLPARABEN; DIMETHYL CAPRAMIDE; GLYCERYL MONOSTEARATE; ISOBUTYLPARABEN; NASTURTIUM OFFICINALE; COMFREY LEAF; CHAMOMILE; CALENDULA OFFICINALIS FLOWER

Cortex Sun X Multi-Pack SPF 30 Thick

ACTIVE INGREDIENTS

Avobenzone 1.0%

Homosalate 5.0%

Octinoxate 7.5%

Octisalate 5.0%

Oxybenzone 6.0%

PURPOSE

Sunscreen

Sunscreen

Sunscreen

Sunscreen

Sunscreen

USES

helps prevent sunburn

If used as directed with other sun protection measures (see Directions) decreases the risk of skin cancer and early skin aging caused by the sun.

WARNINGS

For external use only

Do Not Use

- on damaged or broken skin

When using this product

- keep out of the eyes
- rinse with water to remove

Stop use and aska doctor if

- rash occurs

Keep out of reach of children

If swallowed get medical help or contact a Poison Control center right away.

DIRECTIONS

- apply liberally and evenly 15 minutes before sun exposure
- Sun Protection Measures: spending time in the sun increases your risk of skin cancer and early skin aging. To decrease this risk, regularly use a sunscreen with a broad spectrum SPF value of 15 or higher and after sun protection measures including:
- limit time in the sun, especially from 10:00 a.m. - 2 p.m.
- wear long-sleeved shirts, pants, hats and sunglasses.
- reapply:
- after 80 minutes of swimming or sweating
- immediately after towel drying
- at least every 2 hours
- children under 6 months of age: Ask a doctor

OTHER INFORMATION

- protect this product from excessive heat or direct sun

INACTIVE INGREDIENTS

acrylates/C10-30 alkyl acrylate crosspolymer, aloe barbadensis leaf juice, butylparaben, calendula officinalis flower extract, carbomer, chamomile recutita extract, dimethicone, dimethyl capramide, ethylparaben, fragrance, glyceryl stearate, isobutylparaben, methylparaben, nasturtium officinale extract, peg-100 stearate, phenoxyethanol, propylparaben, symphytum officinale leaf extract, tetrasodium EDTA, triethanolamine, tocopherol, tocopherol acetate, water

QUESTIONS?

Call 1-877-684-5774

Kit Contents

1 Towelette